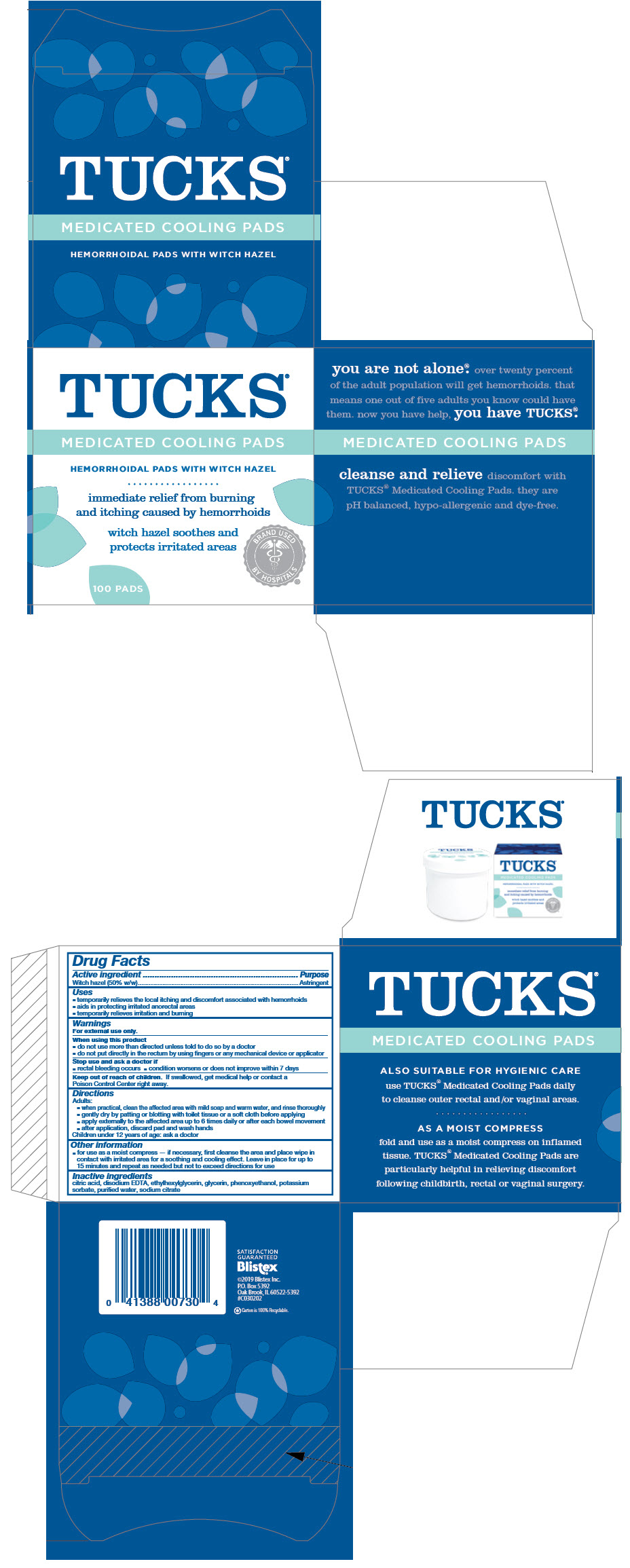 DRUG LABEL: Tucks Medicated Cooling Pads
NDC: 10157-2103 | Form: SOLUTION
Manufacturer: Blistex Inc
Category: otc | Type: HUMAN OTC DRUG LABEL
Date: 20241213

ACTIVE INGREDIENTS: WITCH HAZEL 500 mg/1 mL
INACTIVE INGREDIENTS: WATER; GLYCERIN; SODIUM CITRATE, UNSPECIFIED FORM; CITRIC ACID MONOHYDRATE; ETHYLHEXYLGLYCERIN; PHENOXYETHANOL; EDETATE DISODIUM; POTASSIUM SORBATE

Tucks ® Medicated Cooling Pads

Drug Facts

Active ingredient

Witch hazel (50% w/w)

Purpose

Astringent

Uses

- temporarily relieves the local itching and discomfort associated with hemorrhoids
- aids in protecting irritated anorectal areas
- temporarily relieves irritation and burning

Warnings

For external use only.

When using this product

- do not use more than directed unless told to do so by a doctor
- do not put directly in the rectum by using fingers or any mechanical device or applicator

Stop use and ask a doctor if

- rectal bleeding occurs
- condition worsens or does not improve within 7 days

Keep out of reach of children. If swallowed, get medical help or contact a Poison Control Center right away.

Directions

Adults:

- when practical, clean the affected area with mild soap and warm water, and rinse thoroughly
- gently dry by patting or blotting with toilet tissue or a soft cloth before applying
- apply externally to the affected area up to 6 times daily or after each bowel movement
- after application, discard pad and wash hands

Children under 12 years of age: ask a doctor

Other information

- for use as a moist compress — if necessary, first cleanse the area and place wipe in contact with irritated area for a soothing and cooling effect. Leave in place for up to 15 minutes and repeat as needed but not to exceed directions for use

Inactive ingredients

citric acid, disodium EDTA, ethylhexylglycerin, glycerin, phenoxyethanol, potassium sorbate, purified water, sodium citrate

PRINCIPAL DISPLAY PANEL - 100 Pad Jar Carton

TUCKS®

MEDICATED COOLING PADS

HEMORRHOIDAL PADS WITH WITCH HAZEL

immediate relief from burning
and itching caused by hemorrhoids

witch hazel soothes and
protects irritated areas

BRAND USED BY HOSPITALS®

100 PADS